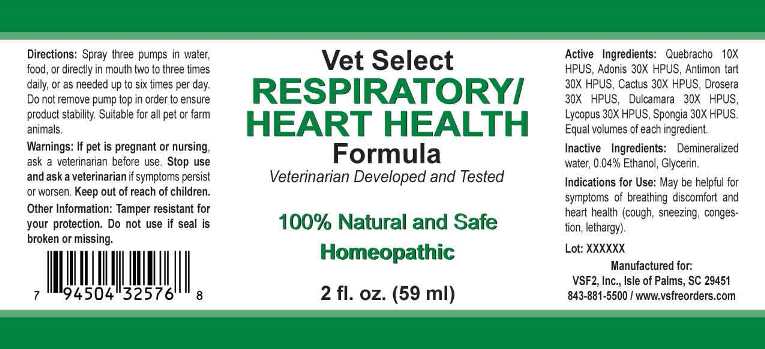 DRUG LABEL: Respiratory/Heart Health
NDC: 86100-0004 | Form: LIQUID
Manufacturer: Vsf2, Inc.
Category: homeopathic | Type: OTC ANIMAL DRUG LABEL
Date: 20221026

ACTIVE INGREDIENTS: ASPIDOSPERMA QUEBRACHO-BLANCO BARK 10 [hp_X]/1 mL; ADONIS VERNALIS 30 [hp_X]/1 mL; ANTIMONY POTASSIUM TARTRATE 30 [hp_X]/1 mL; SELENICEREUS GRANDIFLORUS STEM 30 [hp_X]/1 mL; DROSERA ROTUNDIFOLIA 30 [hp_X]/1 mL; SOLANUM DULCAMARA TOP 30 [hp_X]/1 mL; LYCOPUS VIRGINICUS 30 [hp_X]/1 mL; SPONGIA OFFICINALIS SKELETON, ROASTED 30 [hp_X]/1 mL
INACTIVE INGREDIENTS: WATER; ALCOHOL

Drug Facts:

ACTIVE INGREDIENTS:

Quebracho 10X HPUS, Adonis Vernalis 30X HPUS, Antimonium Tartaricum 30X HPUS, Cactus Grandiflorus 30X HPUS, Drosera (Rotundifolia) 30X HPUS, Dulcamara 30X HPUS, Lycopus Virginicus 30X HPUS, Spongia Tosta 30X HPUS.

INDICATIONS FOR USE:

May be helpful for symptoms of breathing discomfort and heart health (cough, sneezing, congestion, lethargy).

WARNINGS:

If pet is pregnant or nursing, ask a veterinarian before use.

Stop use and ask a veterinarian if symptoms persist or worsen.

Keep out of reach of children.

Other Information: Tamper resistant for your protection. Do not use if seal is broken or missing.

KEEP OUT OF THE REACH OF CHILDREN:

Keep out of reach of children.

DIRECTIONS:

Spray three pumps in water, food, or directly in mouth two to three times daily, or as needed up to six times per day. Do not remove pump top in order to ensure product stability. Suitable for all pet or farm animals.

INDICATIONS FOR USE:

May be helpful for symptoms of breathing discomfort and heart health (cough, sneezing, congestion, lethargy).

INACTIVE INGREDIENTS:

Demineralized water, 0.04% Ethanol, Glycerin.

QUESTIONS:

Manufactured for:

VSF2, Inc., Isle of Palms, SC 29451

843-881-5500 / www.vsfreorders.com

PACKAGE LABEL DISPLAY:

Vet Select

RESPIRATORY/

HEART HEALTH

Formula

Veterinarian Developed and Tested

100% Natural and Safe

Homeopathic